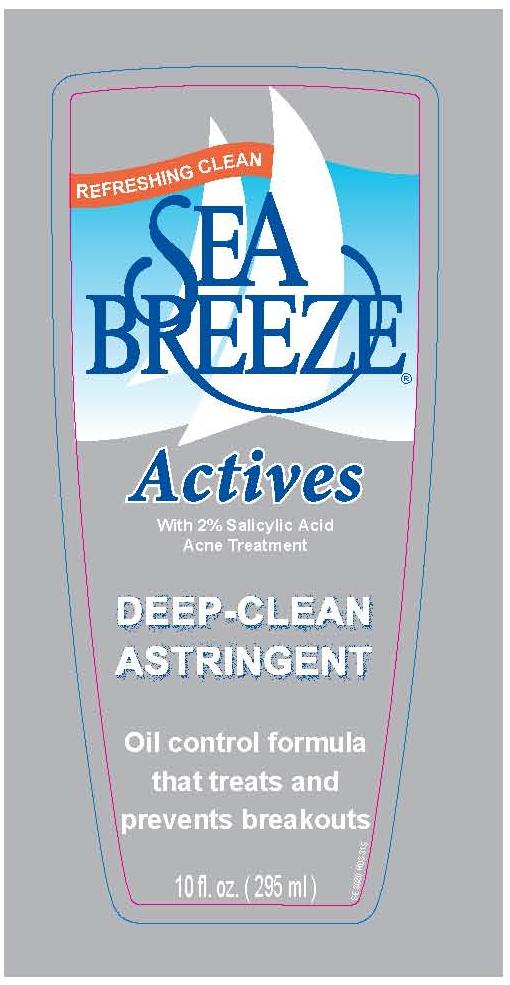 DRUG LABEL: Sea Breeze Actives Deep-Clean Astringent
NDC: 41595-3022 | Form: LIQUID
Manufacturer: Idelle Labs, Ltd
Category: otc | Type: HUMAN OTC DRUG LABEL
Date: 20110419

ACTIVE INGREDIENTS: SALICYLIC ACID 1 g/100 mL
INACTIVE INGREDIENTS: BENZOIC ACID; CAMPHOR (SYNTHETIC); CLOVE OIL; EUCALYPTUS OIL; GLYCERIN; METHYLPROPANEDIOL; D&C ORANGE NO. 4
; PPG-14 BUTYL ETHER

; ALCOHOL; FD&C YELLOW NO. 5
; WATER

Sea Breeze Actives Deep-Clean Astringent

Active ingredient

Salicylic acid 1%

Purpose

Acne medication

Uses

- for the treatment of acne
- clears blackheads

Warnings

For external use only.

When using this product

- and other topical acne medication at the same time or immediately following use of this product, dryness or irritation of the skin may be increased. If this occurs, only one medication should be used unless directed by a doctor.

Keep out of reach of children.

If swallowed, get medical help or contact a Poison Control Center right away.

Flammable,

keep away from open fire or flame.

Directions

- clean skin thoroughly before applying medication.
- moisten a cotton ball and smooth the cotton ball over your face one to three times daily.

Inactive ingredients

Benzoic acid, camphor, clove (eugenia caryophyllus) oil, eucalyptus globulus oil, fragrance, glycerin, methyl propanediol, orange 4, PPG-12-buteth-16, SD alcohol 40-B, yellow 5, water.

Questions or comments?

1-800-487-7273 or visit us at www.seabreezeclean.com

PRINCIPAL DISPLAY PANEL

label